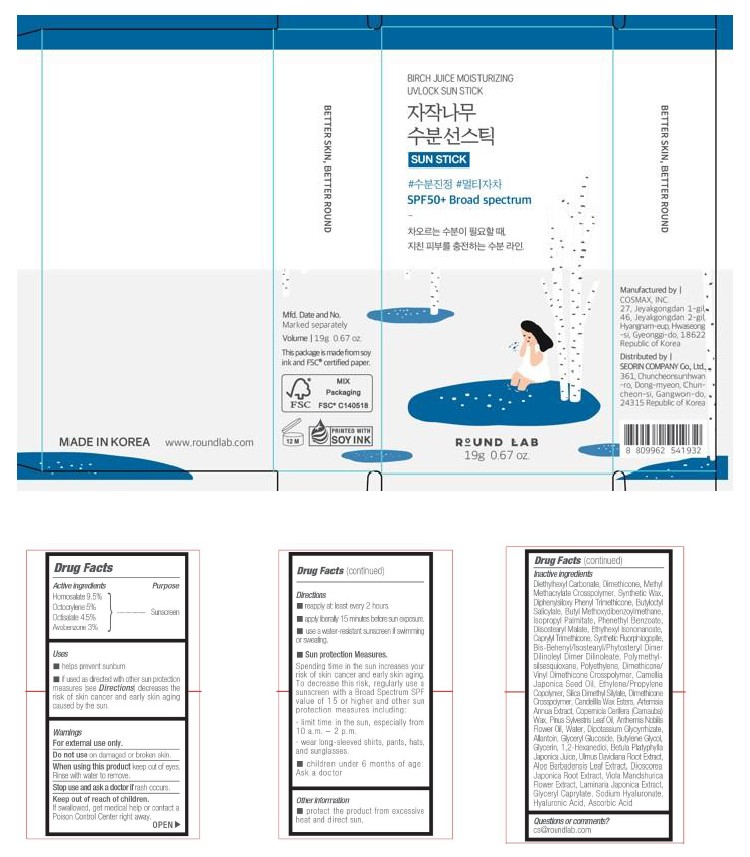 DRUG LABEL: Birch Juice Moisturizing UVLOCK Sunstick SPF 50 Broad Spectrum
NDC: 84616-003 | Form: STICK
Manufacturer: SEORIN COMPANY Co., Ltd.
Category: otc | Type: HUMAN OTC DRUG LABEL
Date: 20241106

ACTIVE INGREDIENTS: OCTOCRYLENE 5 g/100 g; OCTISALATE 4.5 g/100 g; HOMOSALATE 9.5 g/100 g; AVOBENZONE 3 g/100 g
INACTIVE INGREDIENTS: DIETHYLHEXYL CARBONATE; DIMETHICONE; SYNTHETIC WAX (1200 MW); DIPHENYLSILOXY PHENYL TRIMETHICONE; BUTYLOCTYL SALICYLATE; ISOPROPYL PALMITATE; PHENETHYL BENZOATE; DIISOSTEARYL MALATE; ETHYLHEXYL ISONONANOATE; CAPRYLYL TRIMETHICONE; MAGNESIUM POTASSIUM ALUMINOSILICATE FLUORIDE; BIS-BEHENYL/ISOSTEARYL/PHYTOSTERYL DIMER DILINOLEYL DIMER DILINOLEATE; POLYMETHYLSILSESQUIOXANE; POLYETHYLENE; DIMETHICONE/VINYL DIMETHICONE CROSSPOLYMER (SOFT PARTICLE); CAMELLIA JAPONICA SEED OIL; SILICA DIMETHYL SILYLATE; DIMETHICONE CROSSPOLYMER; ARTEMISIA ANNUA LEAF; CARNAUBA WAX; ANTHEMIS NOBILIS FLOWER OIL; WATER; DIPOTASSIUM GLYCYRRHIZATE; ALLANTOIN; GLYCERYL GLUCOSIDE; BUTYLENE GLYCOL; GLYCERIN; 1,2-HEXANEDIOL; BETULA PLATYPHYLLA JAPONICA JUICE; ULMUS DAVIDIANA ROOT; ALOE VERA LEAF; VIOLA MANDSHURICA FLOWER; LAMINARIA JAPONICA; GLYCERYL CAPRYLATE; HYALURONIC ACID; ASCORBIC ACID; CANDELILLA WAX; METHYL METHACRYLATE/GLYCOL DIMETHACRYLATE CROSSPOLYMER; SODIUM HYALURONATE; PINUS SYLVESTRIS LEAF OIL; DIOSCOREA JAPONICA ROOT

Round Lab
Birch Juice Moisturizing
UVLOCK Sun Stick SPF 50+ Broad Spectrum

Active ingredients

Homosalate 9.5%

Octocrylene 5%

Octisalate 4.5%

Avobenzone 3%

Purpose

Sunscreen

Uses

- helps prevent sunburn

- if used as directed with other sun protection measures (see - Directions) decreases the risk of skin cancer and early skin aging caused by the sun.

Warnings

For external use only.

Do not use on damaged or broken skin.

When using this product keep out of eyes. Rinse with water to remove

Stop use and ask a doctor if rash occurs

Keep out of reach of children.

If swallowed, get medical help or contact a Poison Control Center right away.

Do not use on damaged or broken skin

Stop use and ask a doctor if rash occurs

When using this product keep out of eyes. Rinse with water to remove.

Keep out of reach of children

OTHER SAFETY INFORMATION

If swallowed, get medical help or contact a Poison Control Center right away

Directions

- reapply at least every 2 hours.
- apply liberally 15 minutes before sun exposure.
- use a water-resistant sunscreen if swimming or sweating.

• Sun protection Measures.
Spending time in the sun increases your risk of skin cancer and early skin aging.
To decrease this risk, regularly use a sunscreen with a Broad Spectrum SPF value of 15 or higher and other sun protection measures including:
• limit time in the sun, especially from 10 a.m. - 2 p.m.
• wear long-sleeved shirts, pants, hats, and sunglasses.

- children under 6 months of age: Ask a doctor

Other information

protect the product from excessive heat and direct sun

Inactive ingredients

Diethylhexyl Carbonate, Dimethicone, Methyl Methacrylate Crosspolymer, Synthetic Wax, Diphenylsiloxy Phenyl Trimethicone, Butyloctyl Salicylate, Butyl Methoxydibenzoy/methane, Isopropyl Palmitate, Phenethyl Benzoate, Diisostearyl Malate, Ethylhexyl Isononanoate, Capryty Trimethicone, Synthetic Fluorphlogopite, Bis-Behenyl/Isostearyl/Phytosteryl Dimer Dilinoleyl Dimer Dilinoleate, Polymethylsilsesquioxane, Polyethylene, Dimethicone/ Vinyl Dimethicone Crosspolymer, Camellia Japonica Seed Oil, Ethylene/Propylene Copolymer, Silica Dimethyl Silylate, Dimethicone Crosspolymer, Candelilla Wax Esters, Artemisia Annua Extract, Copemicia Cerifera (Camauba) Wax, Pinus Sylvestris Leaf Oil, Anthemis Nobilis Flower Oil, Water, Dipotassium Glycyrrhizate, Allantoin, Glyceryl Glucoside, Butylene Glycol, Glycerin, 1,2-Hexanediol, Betula Platyphylla Japonica Juice, Ulmus Davidiana Root Extract, Aloe Barbadensis Leaf Extract, Dioscorea Japonica Root Extract, Viola Mandshurica Flower Extract, Laminaria Japonica Extract, Glyceryl Caprylate, Sodium Hyaluronate, Hyaluronic Acid, Ascorbic Acid

Questions or comments?

cs@roundlab.com

PACKAGE LABEL

BIRCH JUICE MOISTURIZING

UVLOCK SUN STICK

SUN STICK

SPF50+ Broad Spectrum

ROUND LAB

19g 0.67 oz.